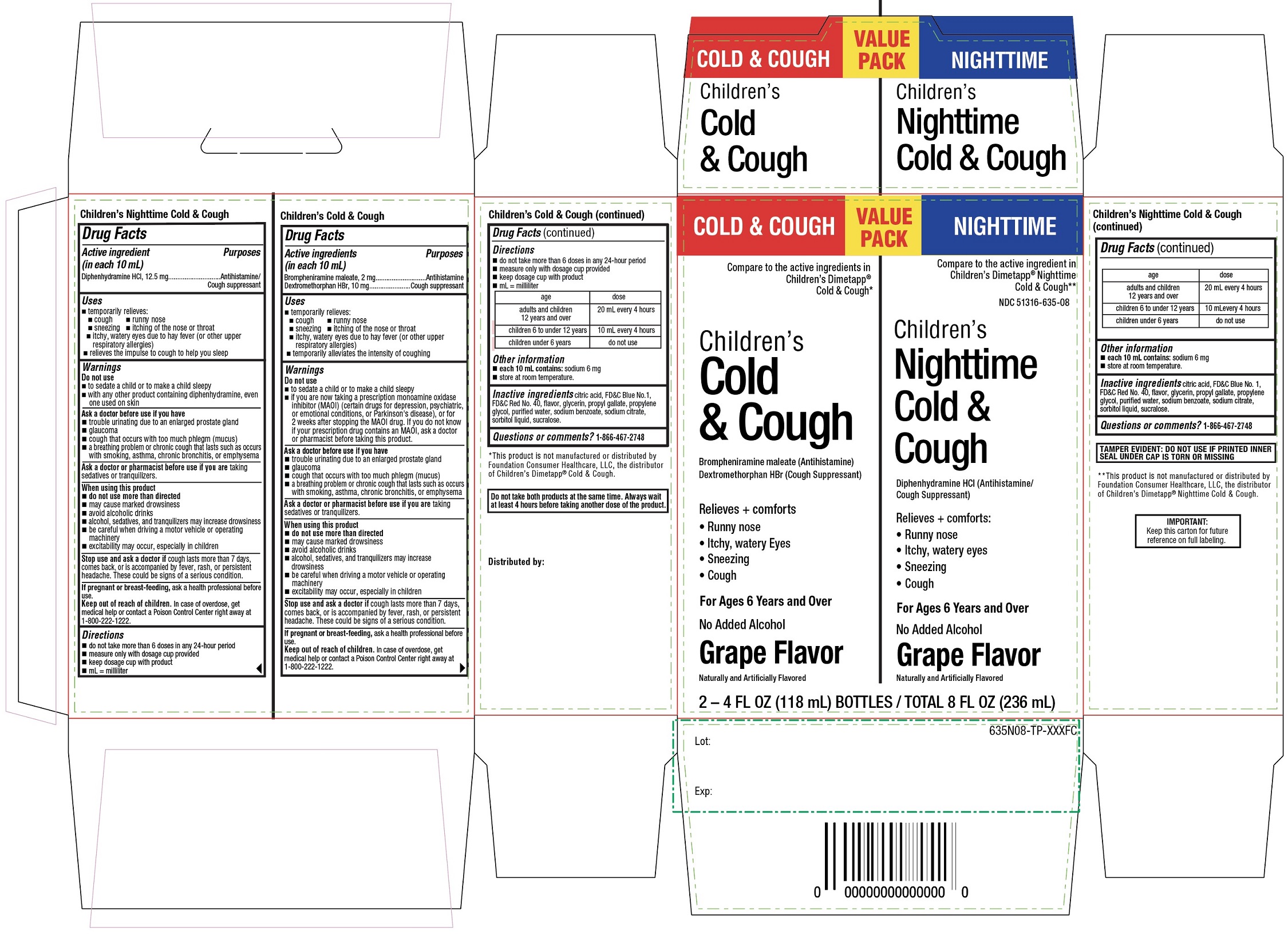 DRUG LABEL: CVS PHARMACY

NDC: 51316-635 | Form: KIT | Route: ORAL
Manufacturer: CVS PHARMACY, INC.
Category: otc | Type: HUMAN OTC DRUG LABEL
Date: 20251210

ACTIVE INGREDIENTS: BROMPHENIRAMINE MALEATE 2 mg/10 mL; DEXTROMETHORPHAN HYDROBROMIDE 10 mg/10 mL; DIPHENHYDRAMINE HYDROCHLORIDE 12.5 mg/10 mL
INACTIVE INGREDIENTS: ANHYDROUS CITRIC ACID; FD&C BLUE NO. 1; FD&C RED NO. 40; GLYCERIN; PROPYL GALLATE; PROPYLENE GLYCOL; WATER; SODIUM BENZOATE; SODIUM CITRATE, UNSPECIFIED FORM; SORBITOL; SUCRALOSE; ANHYDROUS CITRIC ACID; FD&C BLUE NO. 1; FD&C RED NO. 40; GLYCERIN; PROPYL GALLATE; PROPYLENE GLYCOL; WATER; SODIUM BENZOATE; SODIUM CITRATE, UNSPECIFIED FORM; SORBITOL; SUCRALOSE

CVS Children’s Cold & Cough & Children’s Nighttime Cold & Cough Value Pack Drug Facts

Children’s Cold & Cough Active ingredients (in each 10 mL)

Brompheniramine maleate, 2 mg

Dextromethorphan HBr, 10 mg

Children’s NighttimeCold & Cough Active ingredients (in each 10 mL)

Diphenhydramine HCL12.5 mg

Purposes forChildren’s Cold & Cough

Antihistamine

Cough suppressant

Purposes forChildren’s NighttimeCold & Cough

Antihistamine/Cough suppressant

Uses

Cold & Cough

- temporarily relieves
  - runny nose
  - cough
  - sneezing
  - itching of the nose or throat
  - itchy, watery eyes due to hay fever (or other upper respiratory allergies)
  - temporarily alleviates the intensity of coughing

Nighttime Cold & Cough

- temporarily relieves
  - runny nose
  - cough
  - sneezing
  - itching of the nose or throat
  - itchy, watery eyes due to hay fever (or other upper respiratory allergies)
  - relieves the impulse to cough to help you sleep.

Warnings Do not use

Cold & Cough

- to sedate a child or to make a child sleepy
- if you are now taking a prescription monoamine oxidase inhibitor (MAOI) (certain drugs for depression, psychiatric, or emotional conditions, or Parkinson's disease), or for 2 weeks after stopping the MAOI drug. If you do not know if your child's prescription drug contains an MAOI, ask a doctor or pharmacist before giving this product.

Nighttime Cold & Cough

- to sedate a child or to make a child sleepy
- With any other product containing diphenhydramine, even one used on skin

Ask a doctor before use if you have

Cold & Cough

- trouble urinating due to an enlarged prostate gland
- glaucoma
- cough that occurs with too much phlegm (mucus)
- a breathing problem or chronic cough that lasts such as occurs with smoking, asthma, chronic bronchitis, or emphysema.

Nighttime Cold & Cough

- trouble urinating due to an enlarged prostate gland
- glaucoma
- cough that occurs with too much phlegm (mucus)
- a breathing problem or chronic cough that lasts such as occurs with smoking, asthma, chronic bronchitis, or emphysema.

Ask a doctor or pharmacist before use if you are

Cold & Cough

taking sedatives or tranquilizers

Nighttime Cold & Cough

taking sedatives or tranquilizers

When using this product

Cold & Cough

- do not use more than directed.
- may cause marked drowsiness
- avoid alcoholic drinks
- alcohol, sedatives and tranquilizers may increase drowsiness
- be careful when driving a motor vehicle or operating machinery
- excitability may occur, especially in children

Nighttime cold & cough

- do not use more than directed.
- may cause marked drowsiness
- avoid alcoholic drinks
- alcohol, sedatives and tranquilizers may increase drowsiness
- be careful when driving a motor vehicle or operating machinery
- excitability may occur, especially in children

Stop use and ask a doctor if

Cold & Cough

cough lasts more than 7 days, comes back, or is accompanied by fever, rash, or persistent headache.

These could be signs of a serious condition.

Nighttime cold & cough

cough lasts more than 7 days, comes back, or is accompanied by fever, rash, or persistent headache.

These could be signs of a serious condition.

Keep out of reach of children.

Cold & Cough

In case of overdose, get medical help or contact a Poison Control Center right away at 1-800-222-1222.

Nighttime Cold & Cough

In case of overdose, get medical help or contact a Poison Control Center right away at 1-800-222-1222.

If pregnant or breast-feeding,

Ask a health professional before use

Directions

Cold & Cough

- do not take more than 6 doses in any 24-hour period
- measure only with dosing cup provided.
- Keep dosage cup with product
- mL= milliliter

age | dose
Adults and children 12 years and over | 20 mL every 4 hours
children 6 to under 12 years | 10 mL every 4 hours
children under 6 years | do not use

Nighttime cold & cough

- do not take more than 6 doses in any 24-hour period
- measure only with dosing cup provided.
- Keep dosage cup with product
- mL= milliliter

age | dose
Adults and children 12 years and over | 20 mL every 4 hours
children 6 to under 12 years | 10 mL every 4 hours
children under 6 years | do not use

Other information

Cold & cough

- each 10 mL contains:sodium 6 mg
- store at room temperature.

Nighttime cold & cough

- each 10 mL contains:sodium 6 mg
- store at room temperature.

Inactive ingredients

Inactive ingredients for Cold & Cough

citric acid, FD&C blue #1, FD&C red #40, flavor, glycerin, propyl gallate, propylene glycol, purified water, sodium benzoate, sodium citrate, sorbitol, sucralose

Inactive ingredients for Nighttime

citric acid, FD&C blue #1, FD&C red #40, flavor, glycerin, propyl gallate, propylene glycol, purified water, sodium benzoate, sodium citrate, sorbitol, sucralose

Questions or comments?

1-866-467-2748

Principal Display Panel

Compare to the active ingredients in Children's Dimetapp® Cold & Cough*

Children's

Cold & Cough

Brompheniramine Maleate (Antihistamine),

Dextromethorphan HBr (Cough Suppressant)

Relieves + comforts

- Runny nose
- Itchy, watery eyes
- Sneezing
- Cough

For Ages 6 Years and over

No Added Alcohol

Grape Flavor

Naturally and Artificially Flavored

Compare to the active ingredients in Children's Dimetapp® Nighttime Cold & Congestion**

Children's Nighttime

Cold & Cough

Diphenhydramine HCI (Antihistamine / Cough Suppressant)

Relieves + comforts

- Runny nose
- Itchy, watery eyes
- Sneezing
- Cough

For Ages 6 Years and over

No Added Alcohol

Grape Flavor

Naturally and Artificially Flavored

2-4 FL OZ (118 mL) BOTTLES/TOTAL 8 FL OZ (236 mL)

Do not take both products at the same time. Always wait at least 4 hours before taking another dose of the product.

TAMPER EVIDENT: DO NOT USE IF PRINTED INNER SEAL UNDER CAP IS TORN OR MISSING

IMPORTANT:KEEP THIS CARTON FOR FUTURE REFERENCE FOR FULL LABELING

*This product is not manufactured or distributed by Foundation Consumer Healthcare, LLC, the distributor of Children's Dimetapp® Cold & Cough.

**This product is not manufactured or distributed by Foundation Consumer Healthcare, LLC, the distributor of Children's Dimetapp® Nighttime Cold & Cough.

Distributed by: